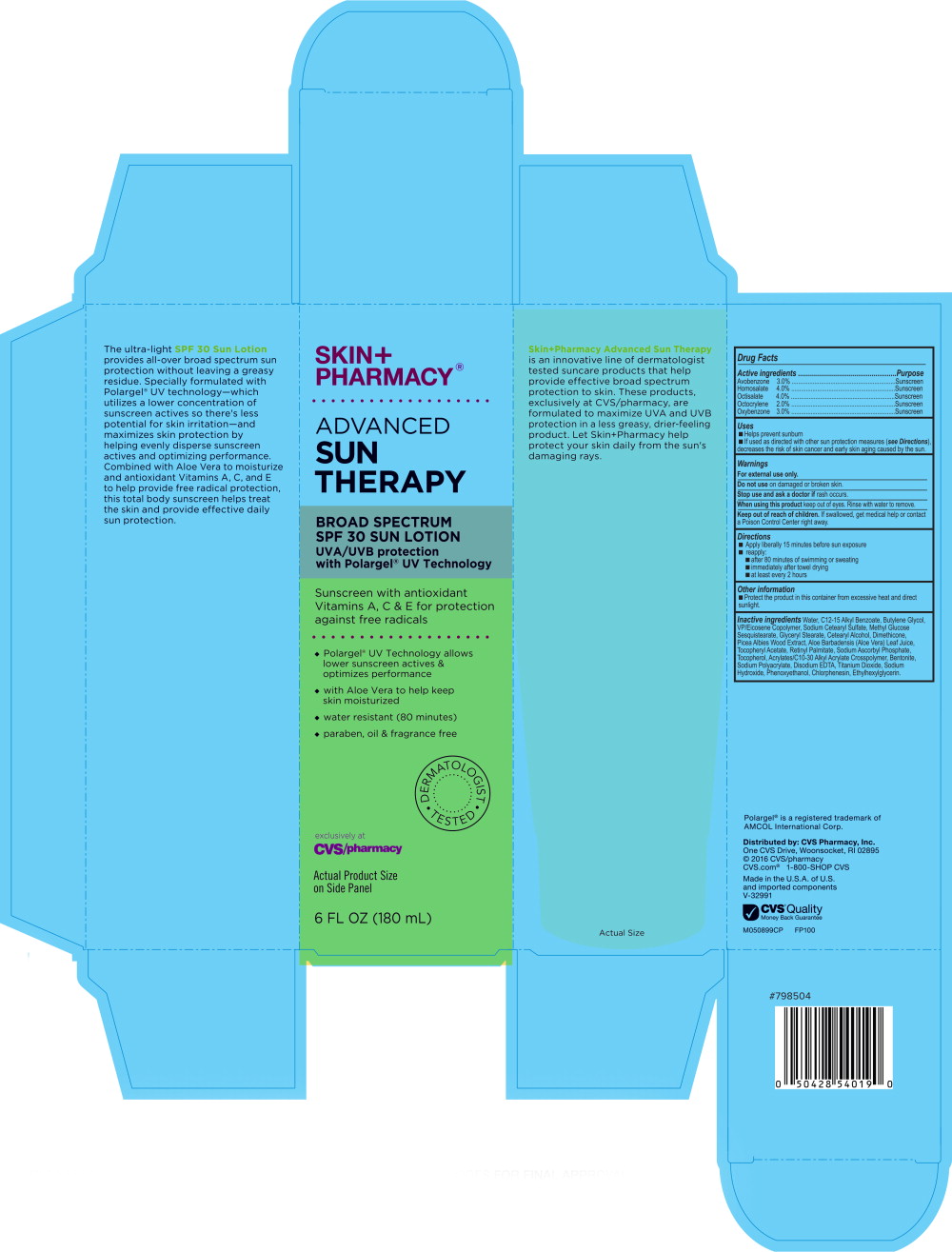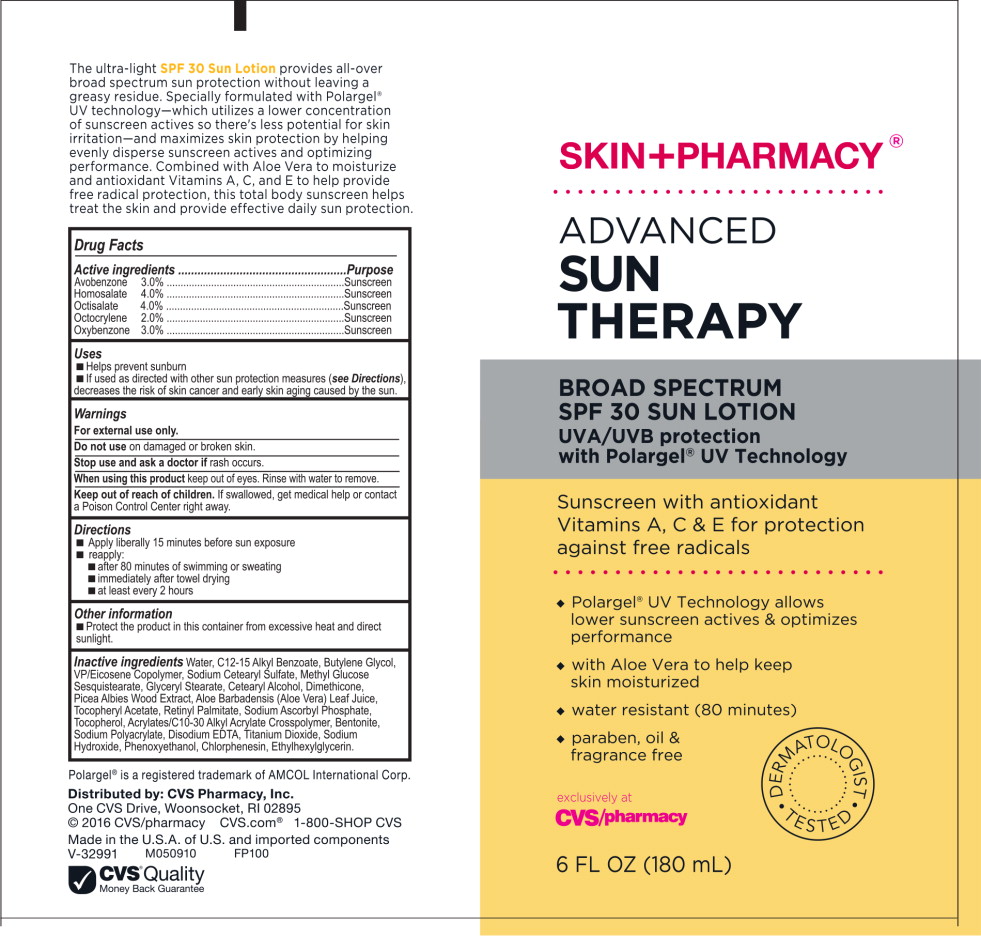 DRUG LABEL: Skin Pharmacy Advanced Sun Therapy Broad Spectrum SPF 30 Sun
NDC: 69842-078 | Form: LIQUID
Manufacturer: CVS Health
Category: otc | Type: HUMAN OTC DRUG LABEL
Date: 20170224

ACTIVE INGREDIENTS: Homosalate 40 mg/1 mL; Octisalate 40 mg/1 mL; Avobenzone 30 mg/1 mL; Oxybenzone 30 mg/1 mL; Octocrylene 20 mg/1 mL
INACTIVE INGREDIENTS: WATER; ALKYL (C12-15) BENZOATE; BUTYLENE GLYCOL; SODIUM CETOSTEARYL SULFATE; GLYCERYL MONOSTEARATE; CETOSTEARYL ALCOHOL; DIMETHICONE; PHENOXYETHANOL; TITANIUM DIOXIDE; SODIUM POLYACRYLATE (8000 MW); BENTONITE; CHLORPHENESIN; PICEA ABIES WOOD; ALOE VERA LEAF; SODIUM HYDROXIDE; ETHYLHEXYLGLYCERIN; .ALPHA.-TOCOPHEROL ACETATE, DL-; EDETATE DISODIUM; SODIUM ASCORBYL PHOSPHATE; VITAMIN A PALMITATE; TOCOPHEROL

Drug Facts

Active ingredients

Avobenzone 3.0%

Homosalate 4.0%

Octisalate 4.0%

Octocrylene 2.0%

Oxybenzone 3.0%

Purpose

Sunscreen

Sunscreen

Sunscreen

Sunscreen

Sunscreen

Uses

- Helps prevent sunburn
- If used as directed with other sun protection measures (see Directions), decreases the risk of skin cancer and early skin aging cause by the sun.

Warnings

For external use only.

Do not use on damaged or broken skin.

Stop use and ask a doctor if rash occurs.

When using this product keep out of eyes. Rinse with water to remove.

Keep out of reach of children. If swallowed, get medical help or contact a Poison Control Center right away.

Directions

- Apply liberally 15 minutes before sun exposure
- reapply:
  - after 80 minutes of swimming or sweating
  - immediately after towel drying
  - at least every 2 hours

Other information

- Protect the product in this container from excessive heat and direct sunlight.

Inactive ingredients

Water, C12-15 Alkyl Benzoate, Butylene Glycol, VP/Eicosene Copolymer, Sodium Cetearyl Sulfate, Methyl Glucose Sesquistearate, Glyceryl Stearate, Cetearyl Alcohol, Dimethicone, Picea Albies Wood Extract, Aloe Barbadensis (Aloe Vera) Leaf Juice, Tocopheryl Acetate, Retinyl Palmitate, Sodium Ascorbyl Phosphate, Tocopherol, Acrylates/C10-30 Alkyl Acrylate Crosspolymer, Bentonite, Sodium Polyacrylamide, Disodium EDTA, Titanium Dioxide, Sodium Hydroxide, Phenoxyethanol, Chlorphenesin, Ethylhexylglycerin.

Polargel® is a registered trademark of AMCOL International Corp.

Distributed by: CVS Pharmacy, Inc.
One CVS Drive, Woonsocket, RI 02895
© 2016 CVS/pharmacy CVS.com® 1-800-SHOP CVS

Made in the U.S.A. of U.S. and imported components
V-32991 M050899CP FP100
CVS® Quality
Money Back Guarantee

Principal Display Panel - Carton Label

SKIN+
PHARMACY®

ADVANCED
SUN
THERAPY

BROAD SPECTRUM
SPF 30 SUN LOTION

UVA/UVB protection
with Polargel® UV Technology

Sunscreen with antioxidant
Vitamins A, C & E for protection
against free radicals

♦ Polargel® UV Technology allows
  lower sunscreen actives &
  optimizes performance
♦ with Aloe Vera to help keep
  skin moisturized
♦ water resistant (80 minutes)
♦ paraben, oil & fragrance free

DERMATOLOGIST TESTED

exclusively at

CVS/pharmacy

Actual Product Size
on Side Panel

6 FL OZ (180 mL)

Principal Display Panel - Tube Label

SKIN+PHARMACY®

ADVANCED
SUN
THERAPY

BROAD SPECTRUM
SPF 30 SUN LOTION

UVA/UVB protection
with Polargel® UV Technology

Sunscreen with antioxidant
Vitamins A, C & E for protection
against free radicals

♦ Polargel® UV Technology allows
  lower sunscreen actives & optimizes
  performance
♦ with Aloe Vera to help keep
  skin moisturized
♦ water resistant (80 minutes)
♦ paraben, oil &
  fragrance free

DERMATOLOGIST TESTED

exclusively at
CVS/pharmacy

6 FL OZ (180 mL)